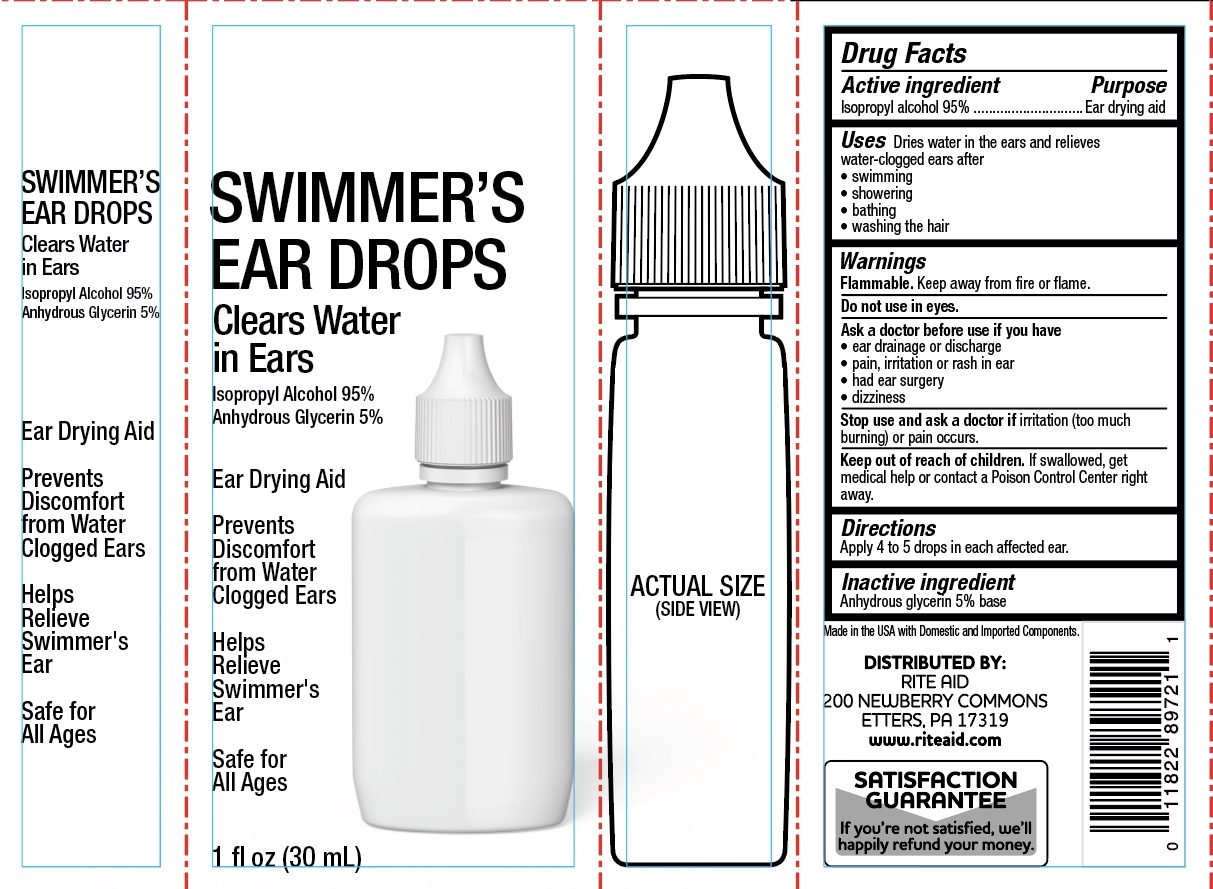 DRUG LABEL: Rite Aid Swimmers Ear Drops
NDC: 11822-1076 | Form: LIQUID
Manufacturer: Rite Aid
Category: otc | Type: HUMAN OTC DRUG LABEL
Date: 20240229

ACTIVE INGREDIENTS: ISOPROPYL ALCOHOL 95 g/100 mL
INACTIVE INGREDIENTS: PROPYLENE GLYCOL; GLYCERIN

Rite Aid Swimmer's Ear Drops

ACTIVE INGREDIENT

Isopropyl Alcohol 95%

PURPOSE

Ear drying aid

INDICATIONS AND USAGE

Dries water in the ears and relieves water-clogged ears after

- swimming
- showering
- bathing
- washing the hair

WARNINGS

Flammable. Keep away from fire or flame.

Do not use in eyes.

Ask a doctor before use if you have

- ear drainage or discharge
- pain, irritation, or rash in the ear
- had ear surgery
- dizziness

Stop use and ask a doctor if irritation (too much burning) or pain occurs

KEEP OUT OF REACH OF CHILDREN

If product is swallowed, get medical help or contact a Poison Control Center right away.

DOSAGE AND ADMINISTRATION

Apply 4 to 5 drops in each affected ear.

INACTIVE INGREDIENT

Anhydrous glycerin 5% base